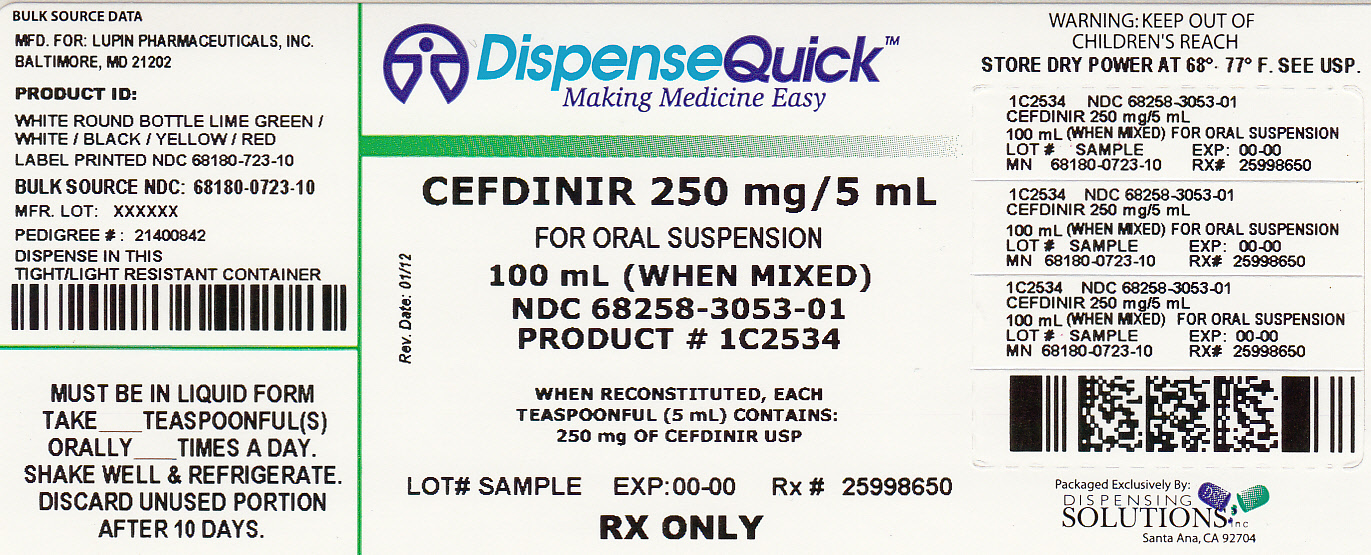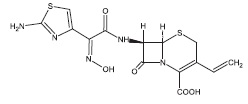 DRUG LABEL: Cefdinir
NDC: 68258-3053 | Form: POWDER, FOR SUSPENSION
Manufacturer: Dispensing Solutions, Inc.
Category: prescription | Type: HUMAN PRESCRIPTION DRUG LABEL
Date: 20120214

ACTIVE INGREDIENTS: CEFDINIR 250 mg/5 mL
INACTIVE INGREDIENTS: CITRIC ACID MONOHYDRATE; COLLOIDAL SILICON DIOXIDE; GUAR GUM; SODIUM BENZOATE; SODIUM CITRATE; STRAWBERRY; SUCROSE; XANTHAN GUM

Cefdinir for Oral Suspension USP

125 mg/5 mL and 250 mg/5 mL
Rx only
To reduce the development of drug-resistant bacteria and maintain the effectiveness of cefdinir for oral suspension and other antibacterial drugs, cefdinir for oral suspension should be used only to treat or prevent infections that are proven or strongly suspected to be caused by bacteria.

DESCRIPTION

Cefdinir for oral suspension contains the active ingredient cefdinir, an extended-spectrum, semisynthetic cephalosporin, for oral administration. Chemically, cefdinir is [6R-[6α,7β(Z)]]-7-[[(2-amino-4- thiazolyl)(hydroxyimino)acetyl]amino]-3-ethenyl-8-oxo-5-thia-1-azabicyclo[4.2.0]oct-2-ene-2-carboxylic acid. Cefdinir is a white to slightly brownish-yellow solid. It is slightly soluble in dilute hydrochloric acid and sparingly soluble in 0.1 M pH 7.0 phosphate buffer. The molecular formula is C14H13N5O5S2 and the molecular weight is 395.42. Cefdinir has the structural formula shown below:

Cefdinir

Cefdinir for oral suspension, after reconstitution, contains 125 mg cefdinir per 5 mL or 250 mg cefdinir per 5 mL and the following inactive ingredients: anhydrous citric acid; colloidal silicon dioxide; guar gum; anhydrous sodium citrate; sodium benzoate; strawberry flavour; sucrose; and xanthan gum.

INDICATIONS AND USAGE

To reduce the development of drug-resistant bacteria and maintain the effectiveness of cefdinir for oral suspension and other antibacterial drugs, cefdinir for oral suspension should be used only to treat or prevent infections that are proven or strongly suspected to be caused by susceptible bacteria. When culture and susceptibility information are available, they should be considered in selecting or modifying antibacterial therapy. In the absence of such data, local epidemiology and susceptibility patterns may contribute to the empiric selection of therapy.

Cefdinir for oral suspension is indicated for the treatment of patients with mild to moderate infections caused by susceptible strains of the designated microorganisms in the conditions listed below.

Adults and Adolescents:

Enter section text here

Pediatric Patients:

Enter section text here

CONTRAINDICATIONS

Cefdinir is contraindicated in patients with known allergy to the cephalosporin class of antibiotics.

WARNINGS

BEFORE THERAPY WITH CEFDINIR IS INSTITUTED, CAREFUL INQUIRY SHOULD BE MADE TO DETERMINE WHETHER THE PATIENT HAS HAD PREVIOUS HYPERSENSITIVITY REACTIONS TO CEFDINIR, OTHER CEPHALOSPORINS, PENICILLINS, OR OTHER DRUGS. IF CEFDINIR IS TO BE GIVEN TO PENICILLIN-SENSITIVE PATIENTS, CAUTION SHOULD BE EXERCISED BECAUSE CROSS-HYPERSENSITIVITY AMONG β-LACTAM ANTIBIOTICS HAS BEEN CLEARLY DOCUMENTED AND MAY OCCUR IN UP TO 10% OF PATIENTS WITH A HISTORY OF PENICILLIN ALLERGY. IF AN ALLERGIC REACTION TO CEFDINIR OCCURS, THE DRUG SHOULD BE DISCONTINUED. SERIOUS ACUTE HYPERSENSITIVITY REACTIONS MAY REQUIRE TREATMENT WITH EPINEPHRINE AND OTHER EMERGENCY MEASURES, INCLUDING OXYGEN, INTRAVENOUS FLUIDS, INTRAVENOUS ANTIHISTAMINES, CORTICOSTEROIDS, PRESSOR AMINES, AND AIRWAY MANAGEMENT, AS CLINICALLY INDICATED.

Clostridium difficile associated diarrhea (CDAD) has been reported with use of nearly all antibacterial agents, including cefdinir, and may range in severity from mild diarrhea to fatal colitis. Treatment with antibacterial agents alters the normal flora of the colon leading to overgrowth of C. difficile.

C. difficile produces toxins A and B which contribute to the development of CDAD. Hypertoxin producing strains of C. difficile cause increased morbidity and mortality, as these infections can be refractory to antimicrobial therapy and may require colectomy. CDAD must be considered in all patients who present with diarrhea following antibiotic use. Careful medical history is necessary since CDAD has been reported to occur over two months after the administration of antibacterial agents.

If CDAD is suspected or confirmed, ongoing antibiotic use not directed against C. difficile may need to be discontinued. Appropriate fluid and electrolyte management, protein supplementation, antibiotic treatment of C. difficile, and surgical evaluation should be instituted as clinically indicated.

OVERDOSAGE

Information on cefdinir overdosage in humans is not available. In acute rodent toxicity studies, a single oral 5600 mg/kg dose produced no adverse effects. Toxic signs and symptoms following overdosage with other β-lactam antibiotics have included nausea, vomiting, epigastric distress, diarrhea, and convulsions. Hemodialysis removes cefdinir from the body. This may be useful in the event of a serious toxic reaction from overdosage, particularly if renal function is compromised.

DOSAGE AND ADMINISTRATION

(see INDICATIONS AND USAGE for Indicated Pathogens)

The recommended dosage and duration of treatment for infections in pediatric patients are described in the following chart; the total daily dose for all infections is 14 mg/kg, up to a maximum dose of 600 mg per day. Once-daily dosing for 10 days is as effective as BID dosing. Once-daily dosing has not been studied in skin infections; therefore, cefdinir for oral suspension should be administered twice daily in this infection. Cefdinir for oral suspension may be administered without regard to meals.

Pediatric Patients (Age 6 Months Through 12 Years)
Type of Infection | Dosage | Duration
Acute Bacterial Otitis Media | 7 mg/kg q12h or | 5 to 10 days
 | 14 mg/kg q24h | 10 days
Acute Maxillary Sinusitis | 7 mg/kg q12h or | 10 days
 | 14 mg/kg q24h | 10 days
Pharyngitis/Tonsilitis | 7 mg/kg q12h or | 5 to 10 days
 | 14 mg/kg q24h | 10 days
Uncomplicated Skin and Skin Structure Infections | 7 mg/kg q12h | 10 days

CEFDINIR FOR ORAL SUSPENSION PEDIATRIC DOSAGE CHART
Weight | 125 mg/5 mL | 250 mg/5 mL
9 kg/20 lbs | 2.5 mL q12h or 5 mL q24h | Use 125 mg/5 mL product
18 kg/40 lbs | 5 mL q12h or 10 mL q24h | 2.5 mL q12h or 5 mL q24h
27 kg/60 lbs | 7.5 mL q12h or 15 mL q24h | 3.75 mL q12h or 7.5 mL q24h
36 kg/80 lbs | 10 mL q12h or 20 mL q24h | 5 mL q12h or 10 mL q24h
≥43 kg a/95 lbs | 12 mL q12h or 24 mL q24h | 6 mL q12h or 12 mL q24h

a Pediatric patients who weight ≥43 kg should receive the maximum daily dose of 600 mg.

Patients With Renal Insufficiency:

For adult patients with creatinine clearance less than 30 mL/min, the dose of cefdinir should be 300 mg given once daily.
Creatinine clearance is difficult to measure in outpatients. However, the following formula may be used to estimate creatinine clearance (CLcr) in adult patients. For estimates to be valid, serum creatinine levels should reflect steady-state levels of renal function.
(weight) (140 – age)
Males: CLcr = ————————————
(72) (serum creatinine)
Females: CLcr = 0.85 x above value
where creatinine clearance is in mL/min, age is in years, weight is in kilograms, and serum creatinine is in mg/dL.(3)
The following formula may be used to estimate creatinine clearance in pediatric patients:
body length or height
CLcr = K x ———————————
serum creatinine
where K = 0.55 for pediatric patients older than 1 year(4) and 0.45 for infants (up to 1 year)(5).
In the above equation, creatinine clearance is in mL/min/1.73 m^2, body length or height is in centimeters, and serum creatinine is in mg/dL.
For pediatric patients with a creatinine clearance of less than 30 mL/min/1.73 m^2, the dose of cefdinir should be 7 mg/kg (up to 300 mg) given once daily.

Patients on Hemodialysis:

Hemodialysis removes cefdinir from the body. In patients maintained on chronic hemodialysis, the recommended initial dosage regimen is a 300 mg or 7 mg/kg dose every other day. At the conclusion of each hemodialysis session, 300 mg (or 7 mg/kg) should be given. Subsequent doses (300 mg or 7 mg/kg) are then administered every other day.

Directions for Mixing
Final Concentration | Final Volume (mL) | Amount of Water | Directions
125 mg/5 mL | 60 | 35 mL | Tap bottle to loosen the powder, then add water in 2
 | 100 | 58 mL | portions. Shake well after each aliquot.
250 mg/5 mL | 60 | 35 mL | Tap bottle to loosen the powder, then add water in 2
 | 100 | 58 mL | portions. Shake well after each aliquot.

After mixing, the suspension can be stored at 20°-25°C (68°-77°F). The container should be kept tightly closed, and the suspension should be shaken well before each administration. The suspension may be used for 10 days, after which any unused portion must be discarded.

HOW SUPPLIED

Cefdinir for oral suspension USP, is an off-white to creamish powder formulation that, when reconstituted as directed, contains 125 mg cefdinir/5 mL or 250 mg cefdinir/5 mL. The reconstituted suspension has an off-white to creamish color and strawberry flavor. The powder is available as follows:

125 mg/5 mL:

60 mL bottles NDC 68180-722-20

100 mL bottles NDC 68180-722-10

250 mg/5 mL:

60 mL bottles NDC 68180-723-20

100 mL bottles NDC 68180-723-10

Store dry powder and reconstituted suspension at 20°-25°C (68°-77°F); [see USP Controlled Room Temperature].

REFERENCES

1. National Committee for Clinical Laboratory Standards. Methods for Dilution Antimicrobial Susceptibility Tests for Bacteria That Grow Aerobically, 4th ed. Approved Standard, NCCLS Document M7-A4, Vol 17(2). NCCLS, Villanova, PA, Jan 1997.
2. National Committee for Clinical Laboratory Standards. Performance Standards for Antimicrobial Disk Susceptibility Tests, 6th ed. Approved Standard, NCCLS Document M2-A6, Vol 17(1). NCCLS, Villanova, PA, Jan 1997.
3. Cockcroft DW, Gault MH. Prediction of creatinine clearance from serum creatinine. Nephron, 1976;16:31-41.
4. Schwartz GJ, Haycock GB, Edelmann CM, Spitzer A. A simple estimate of glomerular filtration rate in children derived from body length and plasma creatinine. Pediatrics 1976;58:259-63.
5. Schwartz GJ, Feld LG, Langford DJ. A simple estimate of glomerular filtration rate in full-term infants during the first year of life. J Pediatrics 1984;104:849-54.

Manufactured for:

Lupin Pharmaceuticals, Inc.

Baltimore, Maryland 21202

United States

Manufactured by:

Lupin Limited

Mandideep 462 046

INDIA

Clinistix® and Clinitest® are registered trademarks of Miles Diagnostics.

Tes-tape® is a registered trademark of Lilly.

Revised December 15, 2009 ID#: 218627

PRINCIPAL DISPLAY PANEL

NDC 68258-3053-01